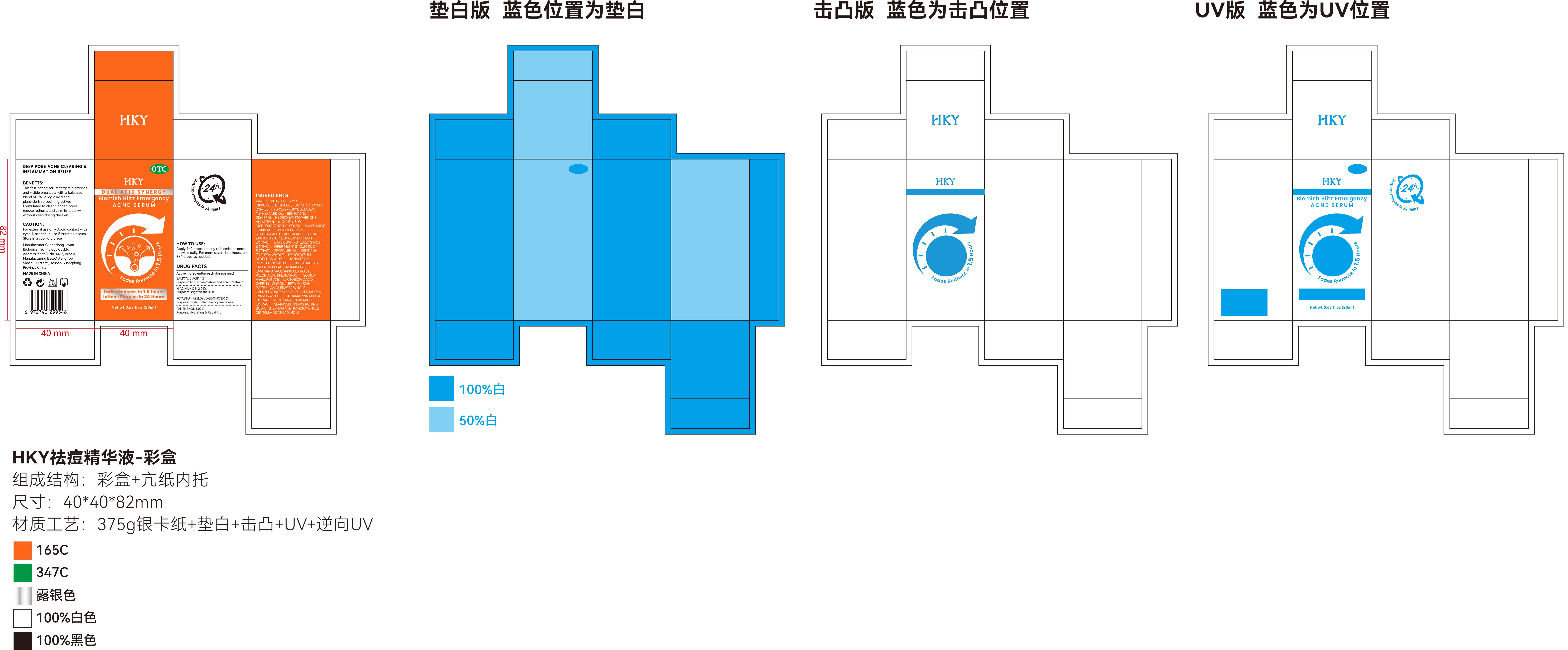 DRUG LABEL: Blemish Blitz Emergency Acne Serum
NDC: 85779-003 | Form: LIQUID
Manufacturer: Guangdong Joyan Biological Technology Co.,Ltd
Category: otc | Type: HUMAN OTC DRUG LABEL
Date: 20250709

ACTIVE INGREDIENTS: SALICYLIC ACID 0.01 g/1 mL
INACTIVE INGREDIENTS: SACCHARIDE ISOMERATE; CENTELLA ASIATICA WHOLE; SOPHORA FLAVESCENS ROOT; GENTIANA TRIFLORA WHOLE; EDETATE DISODIUM; GREEN TEA LEAF; SACCHARINA LATISSIMA; PAEONIA LACTIFLORA ROOT; CAPRYLYL GLYCOL; CENTAUREA CYANUS WHOLE; GENTIANA SCABRA ROOT; PANTHENOL; POTASSIUM AZELOYL DIGLYCINATE; WATER; DIPROPYLENE GLYCOL; KOMAGATAELLA PASTORIS WHOLE; HYDROXYPROPYL BETADEX; DICHLOROBENZYL ALCOHOL; PENTYLENE GLYCOL; RHAMNOSE; TRANSFORMING GROWTH FACTOR BETA RECEPTOR TYPE 3; LACTOBIONIC ACID; STEPHANIA TETRANDRA WHOLE; BENTONITE; PROPANEDIOL; UNDARIA PINNATIFIDA; NIACINAMIDE; BUTYLENE GLYCOL; 1,2-HEXANEDIOL; GLYCERIN; HYDROXYACETOPHENONE; O-CYMEN-5-OL; ZANTHOXYLUM BUNGEANUM FRUIT; CAPSICUM FRUTESCENS FRUIT; HELICHRYSUM STOECHAS WHOLE; TANACETUM PARTHENIUM WHOLE; HYALURONATE SODIUM; CAPRYLHYDROXAMIC ACID; SPARASSIS CRISPA FRUITING BODY; ALLANTOIN; PORTULACA OLERACEA WHOLE; PIPER METHYSTICUM ROOT

85779-003 Blemish Blitz Emergency Acne Serum

ACTIVE INGREDIENT

Salicylic Acid 1%

PURPOSE

Anti-inflammatory and acne treatment

INDICATIONS AND USAGE

DEEP PORE ACNE CLEARING &INFLAMMATION RELIEF
BENEFTS:
This fast-acting serum targets blemishesand visible breakouts with a balancedblend of 1% Salicylic Acid andplant-derived soothing actives.Formulated to clear clogged pores,reduce redness, and calm irritationwithout over-drying the skin.

WARNINGS

For external use only. Avoid contact witheyes. Discontinue use if irritation occurs.Store in a cool, dry place.

KEEP OUT OF REACH OF CHILDREN SECTION

DOSAGE AND ADMINISTRATION

Apply 1-2 drops directly to blemishes onceor twice daily, For more severe breakouts, use3-4 drops as needed.

INACTIVE INGREDIENT

PANTHENOL
NIACINAMIDE
POTASSIUM AZELOYL DIGLYCINATE
WATER
BUTYLENE GLYCOL
DIPROPYLENE GLYCOL
SACCHAROMYCES LYSATE
HYDROXYPROPYL BETADEX
1,2-HEXANEDIOL
BENTONITE
GLYCERIN
HYDROXYACETOPHENONE
ALLANTOIN
o-CYMEN-5-OL
DICHLOROBENZYL ALCOHOL
SACCHARIDE ISOMERATE
PENTYLENE GLYCOL
SOPHORA ANGUSTIFOLIA ROOT EXTRACT
ZANTHOXYLUM BUNGEANUM FRUIT EXTRACT
CAPSICUM FRUTESCENS FRUIT EXTRACT
PIPER METHYSTICUM ROOT EXTRACT
PROPANEDIOL
GENTIANA TRIFLORA WHOLE
HELICHRYSUM STOECHAS WHOLE
TANACETUM PARTHENIUM WHOLE
DISODIUM EDTA
GREEN TEA LEAF
RHAMNOSE
LAMINARIA SACCHARINA EXTRACT
PAEONIA LACTIFLORA ROOT
SODIUM HYALURONATE
LACTOBIONIC ACID
CAPRYLYL GLYCOL
BETA-GLUCAN
PORTULACA OLERACEA WHOLE
CAPRYLHYDROXAMIC ACID
CENTAUREA CYANUS WHOLE
UNDARIA PINNATIFIDA EXTRACT
GENTLANASCABR AROOT EXTRACT
SPARASSIS CRISPA FRUITING BODY
STEPHANIA TETRANDRA WHOLE
CENTELLA ASIATICA WHOLE